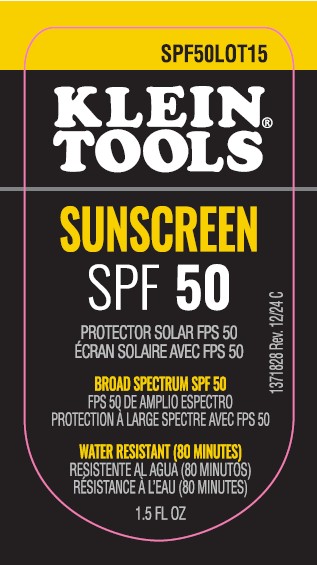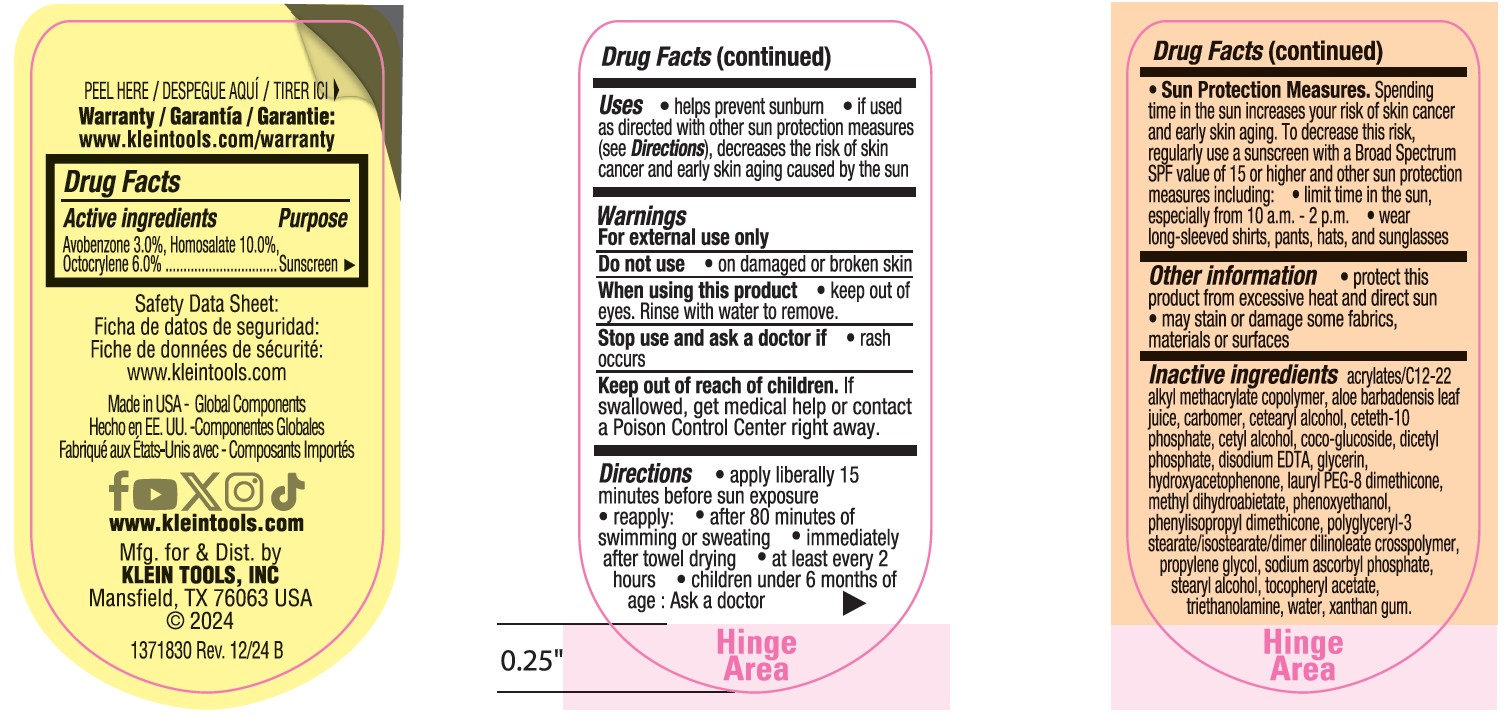 DRUG LABEL: Klein Tools Sunscreen SPF 50
NDC: 85040-001 | Form: LOTION
Manufacturer: KLEIN TOOLS, INC.
Category: otc | Type: HUMAN OTC DRUG LABEL
Date: 20250915

ACTIVE INGREDIENTS: HOMOSALATE 100 mg/1 mL; OCTOCRYLENE 60 mg/1 mL; AVOBENZONE 30 mg/1 mL
INACTIVE INGREDIENTS: WATER; CETOSTEARYL ALCOHOL; STEARYL ALCOHOL; GLYCERIN; BUTYL ACRYLATE/C16-C20 ALKYL METHACRYLATE/METHACRYLIC ACID/METHYL METHACRYLATE COPOLYMER; CETYL ALCOHOL; CARBOMER HOMOPOLYMER TYPE C; CETETH-10 PHOSPHATE; DIHEXADECYL PHOSPHATE; COCO GLUCOSIDE; XANTHAN GUM; EDETATE DISODIUM; METHYL DIHYDROABIETATE; SODIUM ASCORBYL PHOSPHATE; .ALPHA.-TOCOPHEROL ACETATE; ALOE VERA LEAF; PHENOXYETHANOL; TROLAMINE; PROPYLENE GLYCOL; HYDROXYACETOPHENONE

Klein Tools Sunscreen SPF 50 Lotion

Active ingredients

Avobenzone 3.0%, Homosalate 10.0%, Octocrylene 6.0%

Purpose

Sunscreen

Uses

- helps prevent sunburn
- if used as directed with other sun protection measures (see Directions), decreases the risk of skin cancer and early skin aging caused by the sun

Warnings

For external use only

Do not use

• on damaged or broken skin.

When using this product

• keep out of eyes. Rinse with water to remove.

Stop use and ask a doctor if

• rash occurs.

Keep out of reach of children.

If swallowed, get medical help or contact a Poison Control Center right away.

Directions

- apply liberally 15 minutes before sun exposure
- reapply:

• after 80 minutes of swimming or sweating

• immediately after towel drying

• at least every 2 hours

- children under 6 months of age: Ask a doctor
- Sun Protection Measures. Spending time in the sun increases your risk of skin cancer and early skin aging. To decrease this risk, regularly use a sunscreen with a Broad Spectrum SPF value of 15 or higher and other sun protection measures including:

• limit time in the sun, especially from 10 a.m.-2 p.m.

• wear long-sleeved shirts, pants, hats, and sunglasses

Other information

- protect the product in this container from excessive heat and direct sun
- may stain or damage some fabrics/materials or surfaces

Inactive ingredients

acrylates/C12-22 alkyl methacrylate crosspolymer, aloe barbadensis leaf juice, carbomer, cetearyl alcohol, ceteth-10 phosphate, cetyl alcohol, coco-glucoside, dicetyl phosphate, disodium EDTA, glycerin, hydroxyacetophenone, lauryl PEG-8 dimethicone, methyl dihydroabietate, phenoxyethanol, phenylisopropyl dimethicone, polyglyceryl-3 stearate/isostearate/dimer dilinoleate crosspolymer, propylene glycol, sodium ascorbyl phosphate, stearyl alcohol, tocopheryl acetate, triethanolamine, water, xanthan gum.